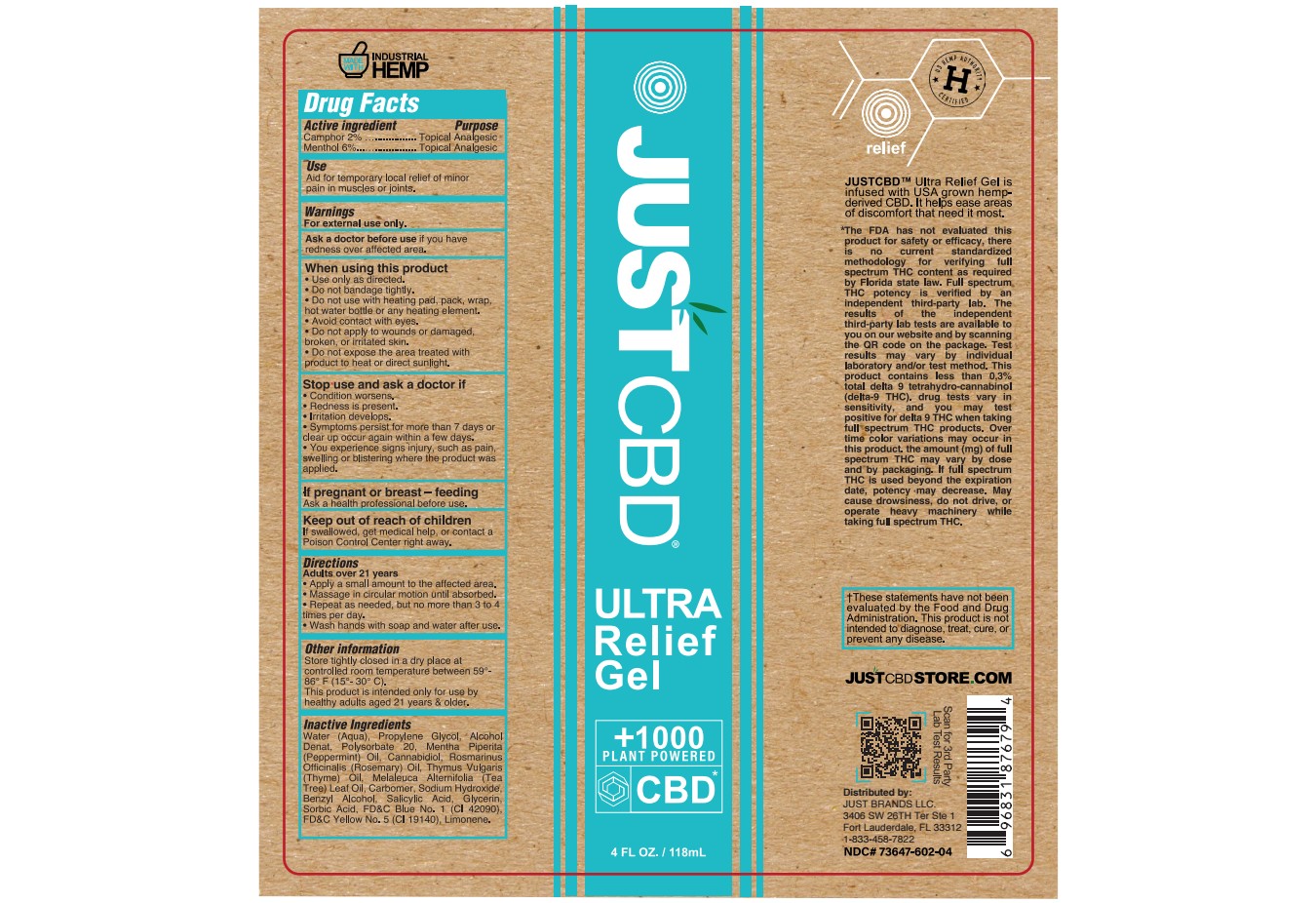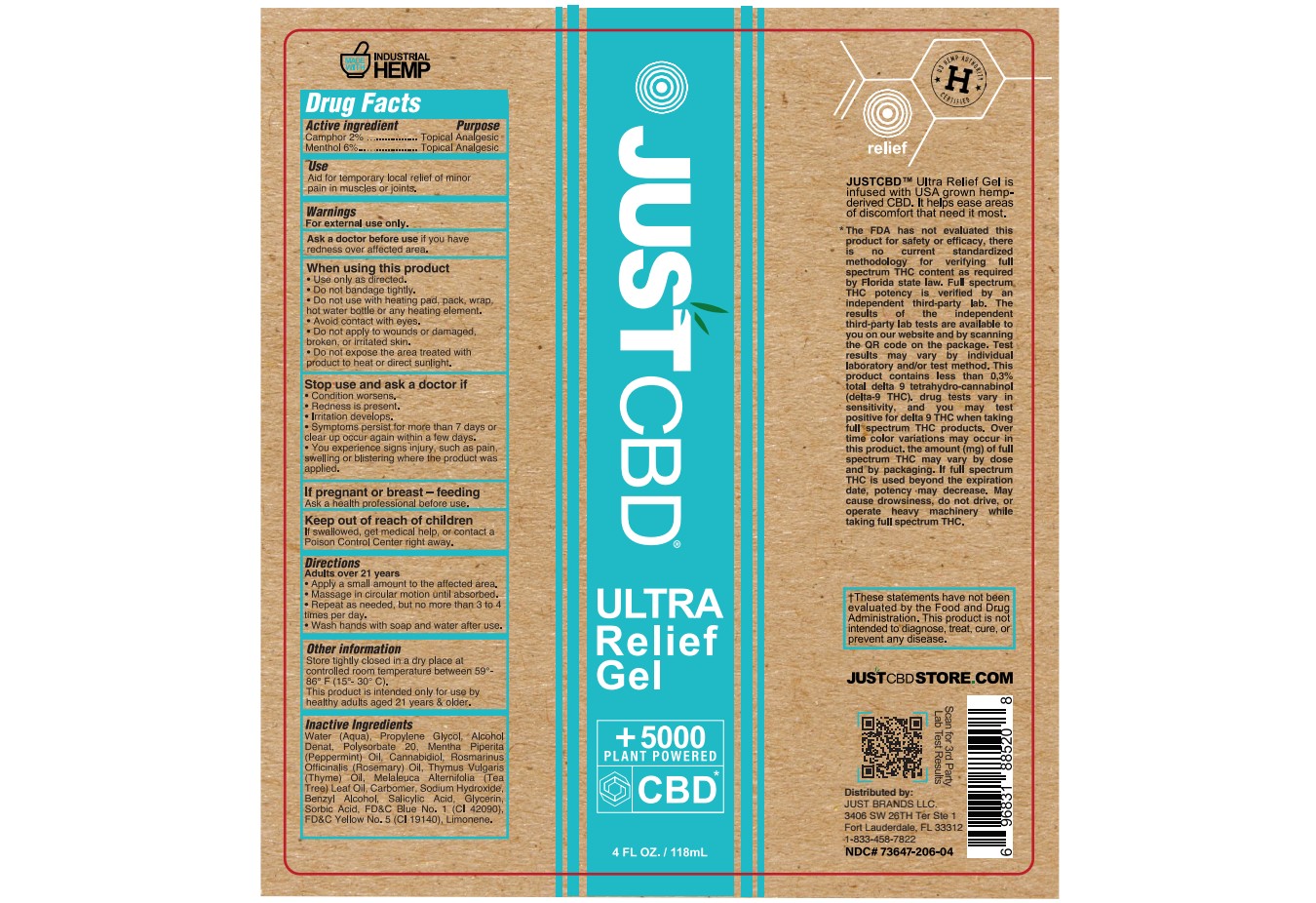 DRUG LABEL: JUST CBD ULTRA RELIEF
NDC: 73647-206 | Form: GEL
Manufacturer: Just Brands LLC
Category: otc | Type: HUMAN OTC DRUG LABEL
Date: 20251117

ACTIVE INGREDIENTS: MENTHOL 6 g/100 mL; CAMPHOR (SYNTHETIC) 2 g/100 mL
INACTIVE INGREDIENTS: CARBOMER 940; WATER; SODIUM HYDROXIDE; MENTHA ARVENSIS LEAF OIL; ROSEMARY OIL; THYME OIL; TEA TREE OIL; BENZYL ALCOHOL; SORBIC ACID; FD&C BLUE NO. 1; FD&C YELLOW NO. 5; ALCOHOL; PROPYLENE GLYCOL; SALICYLIC ACID; GLYCERIN; POLYSORBATE 20; CANNABIDIOL; LIMONENE, (+)-

73647-602-04
73647-206-04

ACTIVE INGREDIENT

Camphor 2%

Menthol 6%

PURPOSE

Topical Analgesic

USE

Aid for temporary local relief of minor pain in muscles or joints.

WARNINGS

For external use only.

ASK DOCTOR

Ask a doctore before use if you have redness over affected area

WHEN USING

Use only as directed.
Do not bandage tightly

Do not use with heating pad, pack, wrap hot water bottle or any heating element.
Avoid contact with eyes.
Do not apply to wounds or damaged, broken, or irritated skin.

Do not expose the area treated with product to heat or direct sunlight.

STOP USE AND ASK A DOCTOR IF:

Condition worsens.
Redness is present.
Irritation develops.
Symptoms persist for more than 7 days or clear up occur again within a few days.

You experience signs injury, such as pain, swelling or blistering where the product was applied.

PREGNANCY OR BREAST FEEDING

Ask a health professional before use.

KEEP OUT OF REACH OF CHILDREN

If swallowed, get medical help or contact a Poison Control Center right away.

DIRECTIONS:

Adults over 21 years:

Apply a small amount to the affected area.
Massage in circular motion until absorbed.
Repeat as needed, but no more than 3 to 4 times per day.

Wash hands with soap and water after use.

OTHER INFORMATION

Store tightly closed in a dry place at controlled temperature between 59°-86° F (15°-30° C).

This product is intended only for use by healthy adults aged 21 years & older.

INACTIVE INGREDIENT

Water (Aqua), Propylene Glycol, Alcohol Denat, Polysorbate 20, Mentha Piperita (Peppermint) Oil, Cannabidiol, Rosmarinus Officinalis (Rosemary) Oil, Thymus Vulgaris (Thyme) Oil, Melaleuca Alternifolia (Tea Tree) Leaf Oil, Carbomer, Sodium Hydroxide, Benzyl Alcohol, Salicylic Acid, Glycerin, Sorbic Acid, FD&C Blue. 1 Powder (CI 42090), FD&C Yellow. 5 (CI 19140), Limonene.